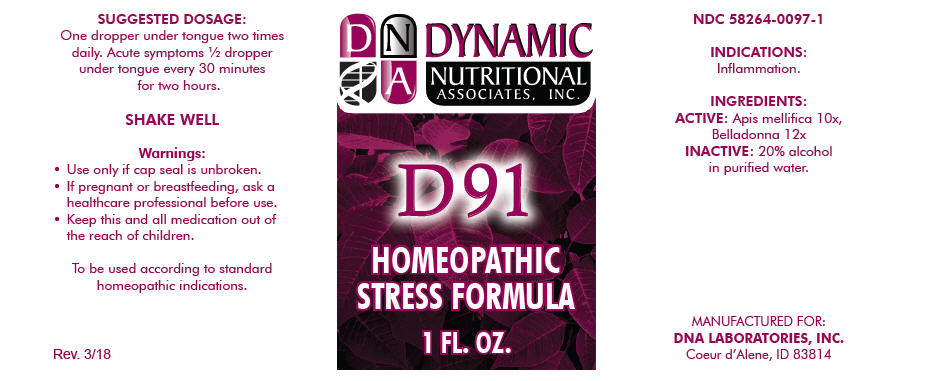 DRUG LABEL: D-91
NDC: 58264-0097 | Form: SOLUTION
Manufacturer: DNA Labs, Inc.
Category: homeopathic | Type: HUMAN OTC DRUG LABEL
Date: 20250113

ACTIVE INGREDIENTS: APIS MELLIFERA 10 [hp_X]/1 mL; ATROPA BELLADONNA 12 [hp_X]/1 mL
INACTIVE INGREDIENTS: ALCOHOL; WATER

D-91

NDC 58264-0097-1

INDICATIONS

PURPOSE

Inflammation.

INGREDIENTS

ACTIVE

Apis mellifica 10x, Belladonna 12x

INACTIVE

20% alcohol in purified water.

SUGGESTED DOSAGE

One dropper under tongue two times daily. Acute symptoms ½ dropper under tongue every 30 minutes for two hours.

STORAGE AND HANDLING

SHAKE WELL

Warnings

- Use only if cap seal is unbroken.

PREGNANCY OR BREAST FEEDING

- If pregnant or breastfeeding, ask a healthcare professional before use.

KEEP OUT OF REACH OF CHILDREN

- Keep this and all medication out of the reach of children.

To be used according to standard homeopathic indications.

PRINCIPAL DISPLAY PANEL - 1 FL. OZ. Bottle Label

DYNAMIC
NUTRITIONAL
ASSOCIATES, INC.

D 91

HOMEOPATHIC
STRESS FORMULA

1 FL. OZ.